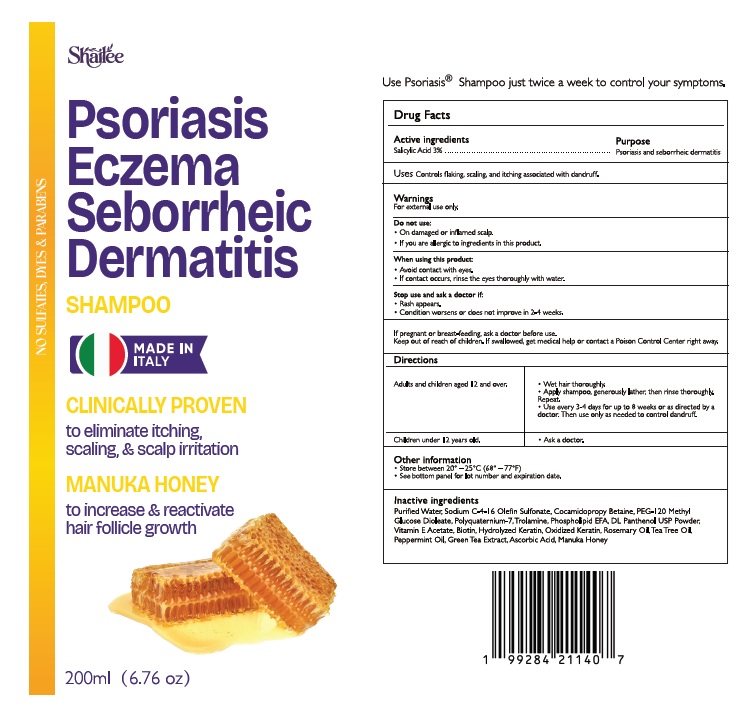 DRUG LABEL: Shailee Psoriasis Treatment
NDC: 84938-008 | Form: LIQUID
Manufacturer: Foshan Sugar Max Cosmetics CO.,Ltd
Category: otc | Type: HUMAN OTC DRUG LABEL
Date: 20251105

ACTIVE INGREDIENTS: SALICYLIC ACID 3 g/100 mL
INACTIVE INGREDIENTS: WATER; SODIUM C14-16 OLEFIN SULFONATE; COCAMIDOPROPYL BETAINE; PEG-120 METHYL GLUCOSE DIOLEATE; POLYQUATERNIUM-7 (70/30 ACRYLAMIDE/DADMAC; 1600000 MW); TROLAMINE; PANTHENOL; TEA TREE OIL; .ALPHA.-TOCOPHEROL ACETATE; BIOTIN; HYDROLYZED SHEEP WOOL KERATIN (200 MW); ROSEMARY OIL; PEPPERMINT OIL; GREEN TEA LEAF; ASCORBIC ACID

Active ingredient Purpose

Salicylic Acid 3% Psoriasis and Dandruff Seborrheic Dermatitis

Uses

Controls flaking, scaling, and itching associated with dandruff.

Warnings

For external use only

Do not use

- On a damaged or inflamed scalp.
- If you are allergic to ingredients in this product.

When using this product

- Avoid contact with the eyes.
- If contact occurs, rinse the eyes thoroughly with water.

Stop use and ask a doctor if

- Rash appears.
- condition worsens or does not improve in 2-4 weeks.

If pregnant or breast-feeding, ask a doctor before use.

Keep out of reach of children. If swallowed, get medical help or contact a Poison Control Center right away.

Directions

Adults and children aged 12 and over. | - Wet hair thoroughly. - Apply shampoo, generously lather, then rinse thoroughly. - Repeat. Use every 3-4 days for up to 8 weeks or as directed by a doctor. Then use only as needed to control dandruff.
Children under 12 years old. | - Ask a doctor.

Other information

- store between 20° – 25°C (68° – 77°F)
- See bottom panel for lot number and expiration date

Inactive ingredients

Purified Water, Sodium C-4-16 Olefin Sulfonate, Cocamidopropyl Betaine, PEG-120 Methyl Glucose Dioleate, Polyquaternium-7, Trolamine, Phospholipid EFA, DL Panthenol USP Powder, Vitamin E Acetate, Biotin, Hydrolyzed Keratin, Oxidized Keratin, Rosemary Oil, Tea Tree Oil, Peppermint Oil,Green Tea Extract, Ascorbic Acid, Manuka Honey